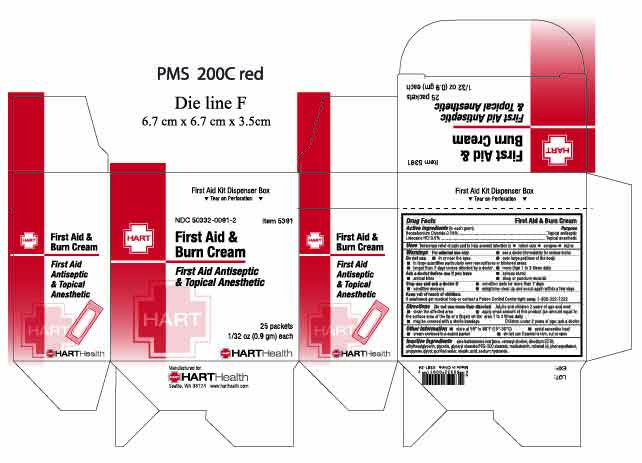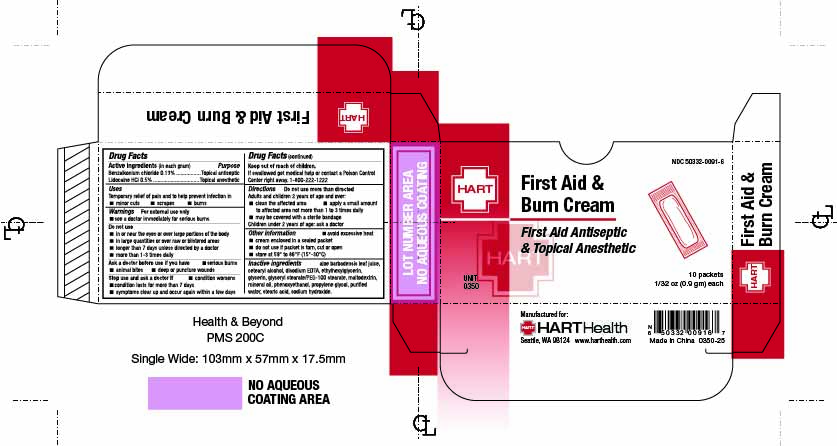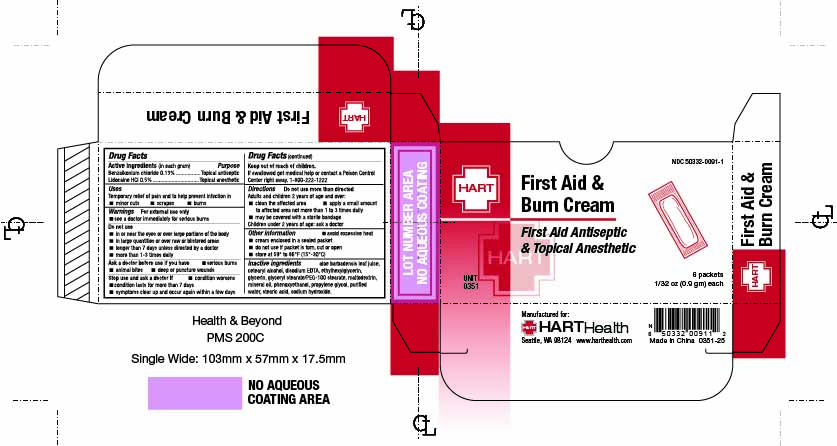 DRUG LABEL: First Aid and Burn
NDC: 50332-0091 | Form: CREAM
Manufacturer: HART Health
Category: otc | Type: HUMAN OTC DRUG LABEL
Date: 20250917

ACTIVE INGREDIENTS: BENZALKONIUM CHLORIDE .13 g/100 g; LIDOCAINE .5 g/100 g
INACTIVE INGREDIENTS: ALOE BARBADENSIS LEAF JUICE; CETEARYL ALCOHOL; DISODIUM HEDTA; ETHYLHEXYLGLYCERIN; GLYCERYL STEARATE/PEG-100 STEARATE; MALTODEXTRIN; MINERAL OIL; PHENOXYETHANOL; PROPYLENE GLYCOL; STEARIC ACID; SODIUM HYDROXIDE; WATER

FIRST AID & BURN CREAM

Active Ingredients (in each gram):

Benzalkonium Chloride 0.13%

Lidocaine HCl 0.5%

Purpose:

Topical Antiseptic

Topical Anesthetic

INDICATIONS AND USAGE

Uses: Temporary relief of pain and to help prevent infection in

- minor cuts
- scrapes
- burns

WARNINGS

Warnings: For external use only. See a doctor immediately for serious burns

Do not use:

- in or near the eyes
- over large portions of the body
- in large quantities particularly over raw surfaces or blistered areas
- longer than 7 days unless directed by a doctor
- more than 1 to 3 times daily

Ask a doctor before use if you have

- serious burns
- animal bites
- deep or puncture wounds

Stop use and ask a doctor if

- condition lasts for more than 7 days
- condition worsens
- symptoms clear up and occur again within a few days

Keep out of reach of children. If swallowed get medical help or contact a Poison Control Center right away. 1-800-222-1222

DOSAGE AND ADMINISTRATION

Directions: do not use more than directed

Adults and children 2 years of age and over:

- clean the affected area
- apply small amount of this product (an amount equal to the surface area of the tip of a finger) on the area 1 to 3 times daily
- may be covered with a sterile bandage

Children under 2 years of age: ask a doctor

INACTIVE INGREDIENT

Inactive Ingredients: aloe barbadensis leaf juice, cetearyl alcohol, disodium EDTA, ethylhexylglycerin, glycerin, glyceryl stearate/PEG-100 stearate, maltodextrin, mineral oil, phenoxyethanol, propylene glycol, purified water, stearic acid, sodium hydroxide.